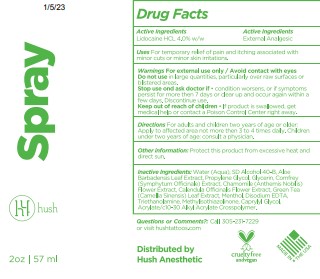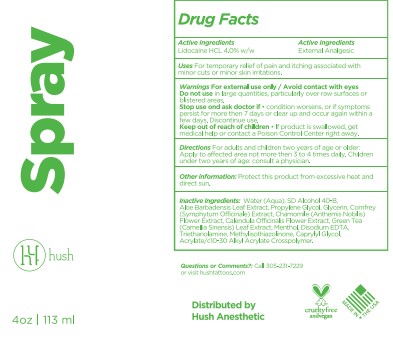 DRUG LABEL: Hush Anesthetic
NDC: 49947-001 | Form: SPRAY
Manufacturer: HUSH Anesthetic
Category: otc | Type: HUMAN OTC DRUG LABEL
Date: 20251110

ACTIVE INGREDIENTS: LIDOCAINE 40 mg/1 g
INACTIVE INGREDIENTS: WATER; ALCOHOL; ALOE VERA LEAF; PROPYLENE GLYCOL; TROLAMINE; GLYCERIN; MENTHOL; CHAMAEMELUM NOBILE FLOWER; CALENDULA OFFICINALIS FLOWER; GREEN TEA LEAF; COMFREY ROOT; CARBOMER INTERPOLYMER TYPE B (ALLYL PENTAERYTHRITOL CROSSLINKED); EDETATE DISODIUM ANHYDROUS; CAPRYLYL GLYCOL; METHYLISOTHIAZOLINONE

Hush Spray

Active Ingredients

Lidocaine HCL 4% w/w

Purpose

Pain Relieving Liquid

Uses

For temporary relief of pain and itching associated with minor cuts or minor skin irritations.

Warnings

For external use only • Avoid contact with eyes

Keep out of reach of children

Stop use and ask a doctor if condition worsens or if symptoms persist for more than 7 days or clear up and occur again with a few days.

Do not use in large quantities, particularly over raw surfaces or blistered areas.

Directions

Adults and children 2 years of age and older: Apply to affected area not more than 3 to 4 times daily. Children under 2 years of age; consult a physician.

Other Information

Protect this product from excessive heat and direct sun.

Inactive ingredients

Acrylates/c10-30 Alkyl Acrylate Crosspolymer, Aloe Barbadensis Leaf Extract, Aqua (Deionized Water), Calendula Officinale Extract, Capyrlyl Glycol, Chamomile (Chamomile Recutita) Extract, Comfrey (Symphytum Officinale) Extract, Disodium EDTA, Glycerin, Green Tea (Camellia Sinensis) Extract, Menthol, Methylisothiazolinone, Propylene Glycol, SD Alcohol 40B, Triethanolamine

Questions or Comments?

Call 305-231-7229 or visit www.hushanesthetic.com